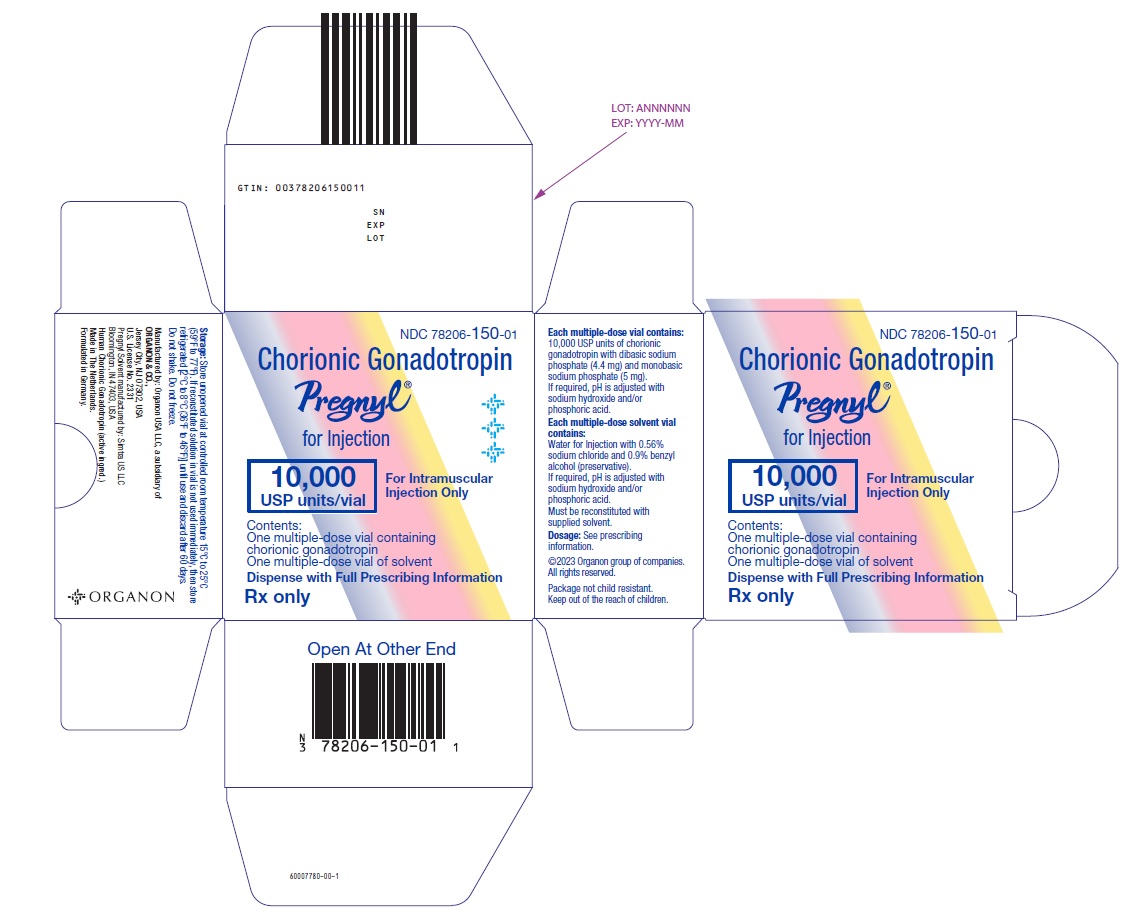 DRUG LABEL: Pregnyl
NDC: 78206-150 | Form: KIT | Route: INTRAMUSCULAR
Manufacturer: Organon LLC
Category: prescription | Type: HUMAN PRESCRIPTION DRUG LABEL
Date: 20251202

ACTIVE INGREDIENTS: CHORIOGONADOTROPIN ALFA 10000 [USP'U]/10 mL
INACTIVE INGREDIENTS: SODIUM PHOSPHATE, MONOBASIC, UNSPECIFIED FORM; SODIUM PHOSPHATE, DIBASIC, UNSPECIFIED FORM; SODIUM HYDROXIDE; PHOSPHORIC ACID; WATER; SODIUM CHLORIDE; BENZYL ALCOHOL

Pregnyl®
(chorionic gonadotropin) for injection

DESCRIPTION

Chorionic gonadotropin, a gonadotropin, is a polypeptide hormone produced by the human placenta and obtained from the urine of pregnant persons. Chorionic gonadotropin is a purified preparation composed of an alpha and a beta subunit. The alpha subunit is essentially identical to the alpha subunits of the human pituitary gonadotropins, luteinizing hormone (LH) and follicle-stimulating hormone (FSH), as well as to the alpha subunit of human thyroid-stimulating hormone (TSH). The beta subunits of these hormones differ in amino acid sequence.

PREGNYL® (chorionic gonadotropin) for injection is a sterile, dried powder for intramuscular injection after reconstitution. Each multiple-dose vial is only for use in one patient and contains 10,000 USP units of chorionic gonadotropin with dibasic sodium phosphate (4.4 mg) and monobasic sodium phosphate (5 mg). If required, pH is adjusted with sodium hydroxide and/or phosphoric acid.

Each package also contains a 10-mL vial of solvent containing: water for injection with 0.56% sodium chloride and 0.9% BENZYL ALCOHOL (preservative), WHICH IS NOT FOR USE IN NEWBORNS. If required, pH is adjusted with sodium hydroxide and/or hydrochloric acid.

CLINICAL PHARMACOLOGY

The action of human chorionic gonadotropin (hCG) is virtually identical to that of pituitary LH, although hCG appears to have a small degree of FSH activity as well. It stimulates production of gonadal steroid hormones by stimulating the interstitial cells (Leydig cells) of the testis to produce androgens and the corpus luteum of the ovary to produce progesterone.

Androgen stimulation in the male leads to the development of secondary sex characteristics and may stimulate testicular descent when no anatomical impediment to descent is present. This descent is usually reversible when hCG is discontinued.

During the normal menstrual cycle, LH participates with FSH in the development and maturation of the normal ovarian follicle, and the mid-cycle LH surge triggers ovulation. hCG can substitute for LH in this function. During a normal pregnancy, hCG secreted by the placenta maintains the corpus luteum after LH secretion decreases, supporting continued secretion of estrogen and progesterone and preventing menstruation.

HCG HAS NO KNOWN EFFECT ON FAT MOBILIZATION, APPETITE OR SENSE OF HUNGER, OR BODY FAT DISTRIBUTION.

INDICATIONS AND USAGE

HCG HAS NOT BEEN DEMONSTRATED TO BE EFFECTIVE ADJUNCTIVE THERAPY IN THE TREATMENT OF OBESITY. THERE IS NO SUBSTANTIAL EVIDENCE THAT IT INCREASES WEIGHT LOSS BEYOND THAT RESULTING FROM CALORIC RESTRICTION, THAT IT CAUSES A MORE ATTRACTIVE OR “NORMAL” DISTRIBUTION OF FAT, OR THAT IT DECREASES THE HUNGER AND DISCOMFORT ASSOCIATED WITH CALORIE-RESTRICTED DIETS.

1. Prepubertal cryptorchidism not due to anatomical obstruction. In general, hCG is thought to induce testicular descent in situations when descent would have occurred at puberty. hCG thus may help predict whether or not orchiopexy will be needed in the future. Although, in some cases, descent following hCG administration is permanent, in most cases, the response is temporary. Therapy is usually instituted in children between the ages of 4 and 9.
2. Selected cases of hypogonadotropic hypogonadism (hypogonadism secondary to a pituitary deficiency) in males.
3. Induction of ovulation and pregnancy in the anovulatory, infertile woman in whom the cause of anovulation is secondary and not due to primary ovarian failure, and who has been appropriately treated with human gonadotropins.

CONTRAINDICATIONS

- Prior hypersensitivity reactions to human gonadotropins, including hCG, or any of the excipients (see ADVERSE REACTIONS).
- High serum FSH, indicating primary gonadal failure in women.
- Presence of uncontrolled non-gonadal endocrinopathies (e.g., thyroid, adrenal, or pituitary disorders).
- Tumors of the hypothalamus or pituitary gland and ovary, breast, or uterus in females and breast or prostate in males.
- Malformations of the reproductive organs incompatible with pregnancy.
- Fibroid tumors of the uterus incompatible with pregnancy.
- Abnormal vaginal bleeding of undetermined origin.

WARNINGS

Use hCG in conjunction with gonadotropin therapy only if the physician is experienced with infertility problems and is familiar with the criteria for patient selection, contraindications, warnings, precautions, and adverse reactions described in the package insert for gonadotropins. Gonadotropin therapy, including hCG, requires a certain time commitment by physicians and supportive health professionals, and requires the availability of appropriate monitoring facilities (see PRECAUTIONS/Laboratory Tests). Safe and effective induction of ovulation with use of PREGNYL requires monitoring of ovarian response with serum estradiol and transvaginal ultrasound on a regular basis.

1. Anaphylaxis
  Anaphylaxis has been reported with urinary-derived hCG products.
2. Ovarian Hyperstimulation Syndrome (OHSS)
  Ovarian Hyperstimulation Syndrome (OHSS) is a medical event distinct from uncomplicated ovarian enlargement and may progress rapidly to become a serious medical event. OHSS is characterized by a dramatic increase in vascular permeability, which can result in a rapid accumulation of fluid in the peritoneal cavity, thorax, and potentially, the pericardium. The early warning signs of the development of OHSS are severe pelvic pain, nausea, vomiting, and weight gain. Abdominal pain, abdominal distension, gastrointestinal symptoms including nausea, vomiting and diarrhea, severe ovarian enlargement, weight gain, dyspnea, and oliguria have been reported with OHSS. Clinical evaluation may reveal hypovolemia, hemoconcentration, electrolyte imbalances, ascites, hemoperitoneum, pleural effusions, hydrothorax, acute pulmonary distress, and thromboembolic reactions. Transient liver function test abnormalities suggestive of hepatic dysfunction with or without morphologic changes on liver biopsy, have been reported in association with OHSS. OHSS occurs after gonadotropin treatment has been discontinued and it can develop rapidly, reaching its maximum about seven to ten days following treatment. Usually, OHSS resolves spontaneously with the onset of menses.
  If there is evidence that OHSS may be developing prior to hCG administration, withhold hCG. Cases of OHSS are more common, more severe, and more protracted if pregnancy occurs; therefore, assess women for the development of OHSS for at least two weeks after hCG administration.
  Severe OHSS may be life-threatening.
  Monitor women undergoing ovarian stimulation for early signs and symptoms of OHSS. Women with known risk factors for a high ovarian response may be especially prone to the development of OHSS during or following treatment with PREGNYL.
  Adherence to the recommended PREGNYL dose and treatment regimen and careful monitoring of ovarian response is important to reduce the risk of OHSS.
  If serious OHSS occurs, stop gonadotropins, including hCG, and consider whether the woman should be hospitalized. Treatment is primarily symptomatic and overall consists of bed rest, fluid and electrolyte management, and analgesics (if needed). Because the use of diuretics can accentuate the diminished intravascular volume, avoid diuretics except in the late phase of resolution.
  Initiate early consultation with a physician experienced in the management of OHSS and fluid and electrolyte imbalances.
3. Pulmonary and Vascular Complications
  Serious pulmonary conditions (e.g., atelectasis, acute respiratory distress syndrome) have been reported in women treated with gonadotropins. In addition, thromboembolic reactions both in association with, and separate from OHSS have been reported following gonadotropin therapy. Intravascular thrombosis, which may originate in venous or arterial vessels, can result in reduced blood flow to vital organs or the extremities. Women with generally recognized risk factors for thrombosis, such as a personal or family history, severe obesity, or thrombophilia, may have an increased risk of venous or arterial thromboembolic events, during or following treatment with gonadotropins. Sequelae of such reactions have included venous thrombophlebitis, pulmonary embolism, pulmonary infarction, cerebral vascular occlusion (stroke), and arterial occlusion resulting in loss of limb and rarely in myocardial infarction. In rare cases, pulmonary complications and/or thromboembolic reactions have resulted in death. In women with recognized risk factors, the benefits of ovulation induction, in vitro fertilization (IVF) or intracytoplasmic sperm injection (ICSI) treatment need to be weighed against the risks. Pregnancy itself also carries an increased risk of thrombosis.
4. Ovarian Torsion
  Ovarian torsion has been reported after treatment with gonadotropins, including PREGNYL. Ovarian torsion may be related to other conditions, such as OHSS, pregnancy, previous abdominal surgery, past history of ovarian torsion, and previous or current ovarian cysts. Damage to the ovary due to reduced blood supply can be limited by early diagnosis and immediate detorsion.
5. Multi-Fetal Gestation and Birth
  Multi-fetal gestation and births have been reported with all gonadotropin therapy including hCG. Advise women of the potential risk of multiple births before starting treatment with gonadotropins including PREGNYL.
6. Congenital Malformations
  The incidence of congenital malformations after ART may be slightly higher than after spontaneous conceptions. This slightly higher incidence is thought to be related to differences in parental characteristics (e.g., maternal age, sperm characteristics) and to the higher incidence of multiple gestations after ART. There are no indications that the use of gonadotropins during ART is associated with an increased risk of congenital malformations.
7. Ectopic Pregnancy
  Infertile women undergoing Assisted Reproductive Technologies (ART) have an increased incidence of ectopic pregnancy. Early ultrasound confirmation that a pregnancy is intrauterine is therefore important.
8. Spontaneous Abortion
  The risk of spontaneous abortion (miscarriage) is increased with gonadotropin products. However, causality has not been established. The increased risk may be a factor of the underlying infertility.
9. Ovarian Neoplasms
  There have been infrequent reports of ovarian neoplasms, both benign and malignant, in women who have undergone multiple drug therapy for ovarian stimulation; however, a causal relationship has not been established.

PRECAUTIONS

1. General
  Induction of androgen secretion by hCG may cause fluid retention.
  Use hCG with caution in patients with cardiac or renal disease, hypertension, epilepsy, migraine, or asthma.
  Careful attention should be given to the diagnosis of infertility in candidates for hCG therapy (see INDICATIONS AND USAGE).
  Evaluate patients for uncontrolled non-gonadal endocrinopathies (e.g., thyroid, adrenal or pituitary disorders) and provide the appropriate specific treatment.
2. Information for Patients
  Prior to therapy with hCG, patients should be informed of the duration of treatment and monitoring of their condition that will be required. The risks of Ovarian Hyperstimulation Syndrome and multiple births in women (see WARNINGS) and other possible adverse reactions (see ADVERSE REACTIONS) should also be discussed.
3. Laboratory Tests
  In most instances, treatment of women with FSH results only in follicular recruitment and development. In the absence of an endogenous LH surge, hCG is given when monitoring of the patient indicates that sufficient follicular development has occurred. This may be estimated by pelvic ultrasound alone or in combination with measurement of serum estradiol levels. The combination of both pelvic ultrasound and serum estradiol measurement are useful for monitoring the development of follicles, for timing of the ovulatory trigger, as well as for detecting ovarian enlargement and minimizing the risk of the Ovarian Hyperstimulation Syndrome and multiple gestation. Confirm the number of growing follicles using ultrasonography because serum estrogens do not give an indication of the size or number of follicles.

Human chorionic gonadotropins can crossreact in the radioimmunoassay of gonadotropins, especially luteinizing hormone. Each individual laboratory should establish the degree of crossreactivity with their gonadotropin assay. Make the laboratory aware that the patient is on hCG, if gonadotropin levels are requested.

The clinical confirmation of ovulation, with the exception of pregnancy, is obtained by direct and indirect indices of progesterone production as well as sonographic evidence of ovulation. The indices most generally used are as follows:

1. A rise in basal body temperature
2. Increase in serum progesterone and
3. Menstruation following a shift in basal body temperature
4. Urinary or serum luteinizing hormone (LH) rise

When used in conjunction with the indices of progesterone production, sonographic visualization of the ovaries will assist in determining if ovulation has occurred. Sonographic evidence of ovulation may include the following:

1. Fluid in the cul-de-sac
2. Collapsed follicle
3. Features consistent with corpus luteum formation (e.g., ovarian stigmata, secretory endometrium)

Accurate interpretation of the indices of ovulation requires a physician who is experienced in the interpretation of these tests.

Sonographic evaluation of the early pregnancy is also important to rule out ectopic pregnancy.

Carcinogenesis, Mutagenesis, Impairment of Fertility

Long-term studies in animals have not been performed to evaluate the carcinogenic or mutagenic potential of chorionic gonadotropin.

Pregnancy

PREGNYL is not indicated in pregnancy. PREGNYL may be used for luteal phase support, but is discontinued upon confirmation of pregnancy. There are no data on the use of hCG in pregnancy.

In the U.S. general population, the estimated background risk of major birth defects and miscarriage in clinically recognized pregnancies is 2% to 4% and 15% to 20%, respectively.

Pediatric Use

Induction of androgen secretion by hCG may induce precocious puberty in pediatric patients treated for cryptorchidism. Discontinue therapy if signs of precocious puberty occur.

Lactation

It is not known whether this drug is excreted in human milk. Because many drugs are excreted in human milk, caution should be exercised if hCG is administered to a nursing woman.

The developmental and health benefits of breastfeeding should be considered along with the mother’s clinical need for PREGNYL and any potential adverse effects on the breastfed child from PREGNYL or from the underlying maternal condition.

Geriatric Use

Clinical studies of PREGNYL (chorionic gonadotropin) for injection did not include subjects aged 65 and over.

ADVERSE REACTIONS

For males and females:
Immune system disorders
Hypersensitivity reactions, both localized and systemic in nature, including anaphylaxis have been reported. In rare cases, generalized rash or fever may occur (see CONTRAINDICATIONS and WARNINGS). If a hypersensitivity reaction is suspected, discontinue PREGNYL and assess for other potential causes for the event.

Psychiatric disorders
Irritability
Restlessness
Depression

Nervous system disorders
Headache

General disorders and administration site conditions
PREGNYL may cause reactions at the site of injection, such as bruising, pain, redness, swelling and itching. Occasionally, allergic reactions have been reported, mostly manifesting as pain and/or rash at the injection site (see CONTRAINDICATIONS and WARNINGS).
Edema
Fatigue

In the female:
Vascular disorders
In rare instances, thromboembolism has been associated with FSH/hCG therapy, usually associated with severe OHSS (see WARNINGS).

Respiratory, thoracic and mediastinal disorders
Hydrothorax, as a complication of severe OHSS (see WARNINGS).

Gastrointestinal disorders
Abdominal pain and gastrointestinal symptoms such as nausea and diarrhea, related to mild OHSS. Ascites, as a complication of severe OHSS (see WARNINGS).

Reproductive system and breast disorders
Unwanted ovarian hyperstimulation, mild or severe Ovarian Hyperstimulation Syndrome (see WARNINGS).
Mild to moderate enlargement of ovaries and ovarian cysts related to mild OHSS. Large ovarian cysts (prone to rupture), usually associated with severe OHSS (see WARNINGS).
Painful breasts

Investigations
Weight gain as a characteristic of severe OHSS (see WARNINGS).

In the male:
Metabolism and nutrition disorders
Water and sodium retention is occasionally seen after administration of high dosages; this is regarded as a result of excessive androgen production.

Reproductive system and breast disorders
HCG treatment may sporadically cause gynecomastia.
Precocious puberty

DOSAGE AND ADMINISTRATION

For intramuscular use only. Each multiple-dose vial is to be used for one patient. The dosage regimen employed in any particular case will depend upon the indication for the use, the age and weight of the patient, and the physician’s preference. The following regimens have been advocated by various authorities:

Prepubertal cryptorchidism not due to anatomical obstruction. Generally, institute therapy in children between the ages of 4 and 9.

1. 4000 USP units 3 times weekly for 3 weeks.
2. 5000 USP units every second day for 4 injections.
3. 15 injections for 500 to 1000 USP units over a period of 6 weeks.
4. 500 USP units 3 times weekly for 4 to 6 weeks. If this course of treatment is not successful, another series is begun 1 month later, giving 1000 USP units per injection.

Selected cases of hypogonadotropic hypogonadism in males.

1. 500 to 1000 USP units 3 times a week for 3 weeks, followed by the same dose twice a week for 3 weeks.
2. 4000 USP units 3 times weekly for 6 to 9 months, following which the dosage may be reduced to 2000 USP units 3 times weekly for an additional 3 months.

Induction of ovulation and pregnancy in the anovulatory, infertile woman in whom the cause of anovulation is secondary and not due to primary ovarian failure and who has been appropriately treated with gonadotropins. (See also prescribing information for gonadotropins for dosage and administration for that drug product.)

5000 to 10,000 USP units 1 day following the last dose of gonadotropins. (A dosage of 10,000 USP units is recommended in the labeling for gonadotropins.)

Directions for Reconstitution

Withdraw sterile air from vial with lyophilized powder and inject into vial with solvent. Remove 1 to 10 mL of solvent and add to vial with lyophilized powder; agitate gently until powder is completely dissolved in solution. Do not shake.

PREGNYL is a white, dry powder / cake. The solvent is a clear and colorless aqueous solution.

Visually inspect parenteral drug products for particulate matter and discoloration prior to administration, whenever solution and container permit. If there is a discoloration or particulates, do not use.

IMPORTANT: IF NEEDED, THE RECONSTITUTED SOLUTION IS STABLE FOR 60 DAYS WHEN REFRIGERATED. DO NOT FREEZE. USE THE RECONSTITUTED SOLUTION WITHIN 60 DAYS OF RECONSTITUTION. IF THE RECONSTITUTED SOLUTION IS NO LONGER NEEDED, DISCARD UNUSED PORTION.

HOW SUPPLIED

Two-vial package containing:
One 10 mL multiple-dose vial for administration by one patient, containing lyophilized powder of 10,000 USP units of chorionic gonadotropin per vial, NDC 78206-150-01.
One 10 mL multiple-dose vial of solvent containing: water for injection with sodium chloride 0.56% and benzyl alcohol (preservative) 0.9%, NDC 78206-151-89.

STORAGE AND HANDLING

Storage: Store unopened vial at controlled room temperature 15°C to 25°C (59°F to 77°F).
If reconstituted solution in vial is not used immediately, then store refrigerated [2°C to 8°C (36°F to 46°F)] until use and discard after 60 days. Do not shake. Do not freeze.

PREGNYL manufactured by:

Organon USA LLC, a subsidiary of
ORGANON & Co.,
Jersey City, NJ 07302, USA

U.S. License No. 2331

PREGNYL Solvent manufactured by:
Simtra US LLC
Bloomington, IN 47403, USA

For patent information: www.organon.com/our-solutions/patent/

© 2025 Organon group of companies. All rights reserved.

Revised: 03/2025

uspi-og8829-pwi-2503r002

Rx only

PRINCIPAL DISPLAY PANEL - Kit Carton

NDC 78206-150-01

Chorionic Gonadotropin

Pregnyl®
for Injection

10,000
USP units/vial

For Intramuscular
Injection Only

Contents:
One multiple-dose vial containing
chorionic gonadotropin
One multiple-dose vial of solvent

Dispense with Full Prescribing Information

Rx only